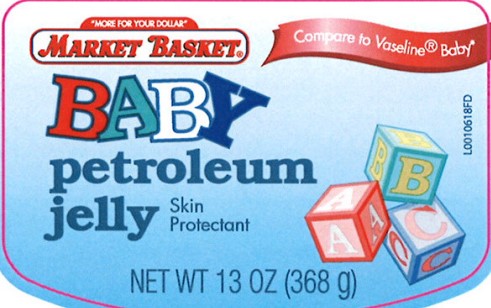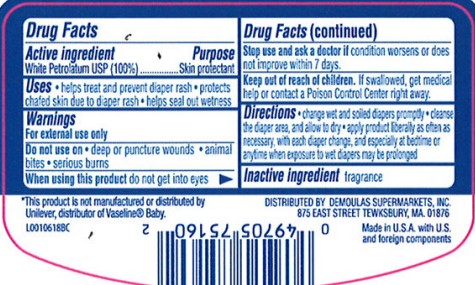 DRUG LABEL: Petroleum
NDC: 53942-519 | Form: JELLY
Manufacturer: Demoulas Super Markets, Inc
Category: otc | Type: HUMAN OTC DRUG LABEL
Date: 20260203

ACTIVE INGREDIENTS: PETROLATUM 100 g/100 g

Market Basket 519.001/519AC-AD
Baby Petroleum Jelly

Active ingredient

White Petrolatum USP (100%)

Purpose

Skin Protectant

Uses

- helps treat and prevent diaper rash
- protects chafed skin due to diaper rash
- helps seal out wetness

Warnings

For external use only

Do not use on

- deep or puncture wounds
- animal bites
- serious burns

When using this product

do not get into eyes.

Stop use and ask a doctor

if condition worsens or does not improve within 7 days

Keep out of reach of children.

If swallowed, get medical help or contact a Poison Control Center right away.

Directions

- change wet and soilded diapers promptly
- cleanse the diaper area, and allow to dry
- apply product liberally as often as necessary, with each diaper change, and especially at bedtime or anytime when exposure to wet diapers may be prolonged

Inactive ingredient

fragrance

Disclaimer

*This product is not manufactured or distributed by Unilever, distributer of Vaseline®Baby.

Adverse reaction

Distributed By Demoulas Supermarkets, Inc

875 East Street Tweksbury, MA 01876

Made in the U.S.A. with U.S. and foreign components

principal display panel

"MORE FOR YOUR DOLLAR"

Compare to Vaseline®Baby*

MARKET BASKET®

BABY

petroleum jelly

Skin Protectant

NET WT 13 oz (368 g)